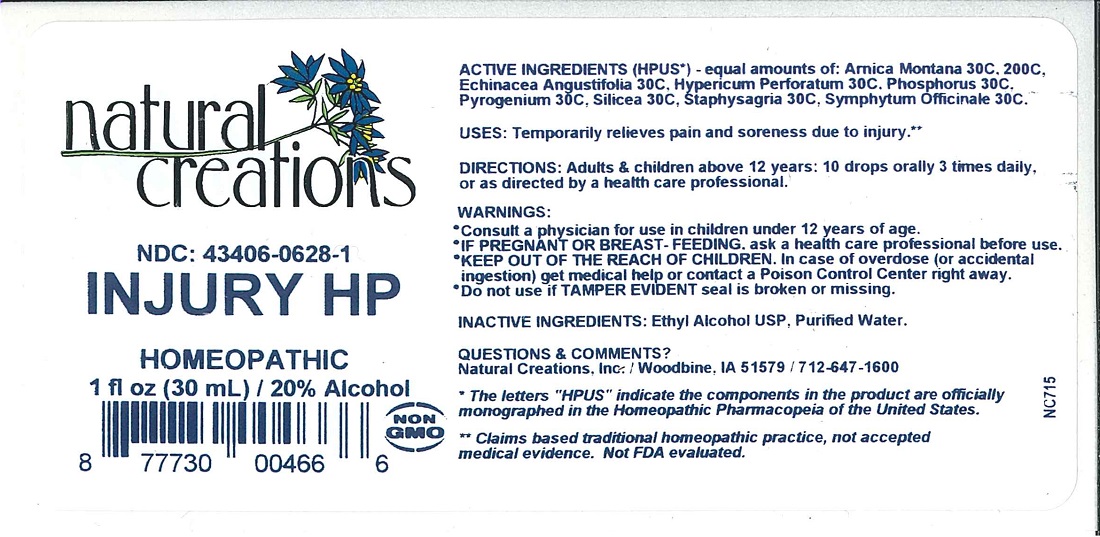 DRUG LABEL: INJURY HP
NDC: 43406-0628 | Form: LIQUID
Manufacturer: Natural Creations, Inc.
Category: homeopathic | Type: HUMAN PRESCRIPTION DRUG LABEL
Date: 20251216

ACTIVE INGREDIENTS: ARNICA MONTANA 200 [hp_C]/1 mL; ECHINACEA ANGUSTIFOLIA 30 [hp_C]/1 mL; HYPERICUM PERFORATUM 30 [hp_C]/1 mL; PHOSPHORUS 30 [hp_C]/1 mL; RANCID BEEF 30 [hp_C]/1 mL; Silicon Dioxide 30 [hp_C]/1 mL; DELPHINIUM STAPHISAGRIA SEED 30 [hp_C]/1 mL; COMFREY ROOT 30 [hp_C]/1 mL
INACTIVE INGREDIENTS: WATER; ALCOHOL

INJURY HP

ACTIVE INGREDIENT

ACTIVE INGREDIENTS (HPUS*) - equal amounts of: Arnica Montana 30C, 200C, Echinacea Angustifolia 30C, Hypericum Perforatum 30C, Phosphorus 30C, Pyrogenium 30C, Silicea 30C, Staphysagria 30C, Symphytum Officinale 30C.

INDICATIONS AND USAGE

USES: Temporarily relieves pain and soreness due to injury.**

WARNINGS:

- Consult a physician for use in children under 12 years of age.
- IF PREGNANT OR BREAST-FEEDING, ask a health care professional before use.
- KEEP OUT OF THE REACH OF CHILDREN. In case of overdose (or accidental ingestion) get medical help or contact a Poison Control Center right away.
- Do not use if TAMPER EVIDENT seal is broken or missing.

DOSAGE AND ADMINISTRATION

DIRECTIONS: Adults and children above 12 years: 10 drops orally 3 times daily, or as directed by a health care professional.

REFERENCES

*The letters "HPUS" indicate the components in the product are officially monographed in the Homeopathic Pharmacopeia of United States.

**Claims based on traditional homeopathic practice, not accepted medical evidence. Not FDA evaluated

INACTIVE INGREDIENTS: Ehtyl Alcohol USP, Purified Water.

QUESTIONS AND COMMENTS?

Natural Creations, Inc. / Woodbine, IA 51579 / 712-647-1600

PURPOSE

USES: Temporarily relieves pain and soreness due to injury.**

KEEP OUT OF REACH OF CHILDREN

KEEP OUT OF THE REACH OF CHILDREN. In case of overdose (or accidental ingestion) get medical help or contact a Poison Control Center.

PACKAGE LABEL

NDC: 43406-0628-1

INJURY HP

HOMEOPATHIC

1 fl oz (30 mL) / 20% Alcohol

UPC: 877730004666